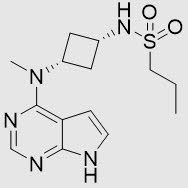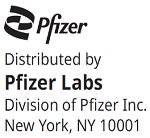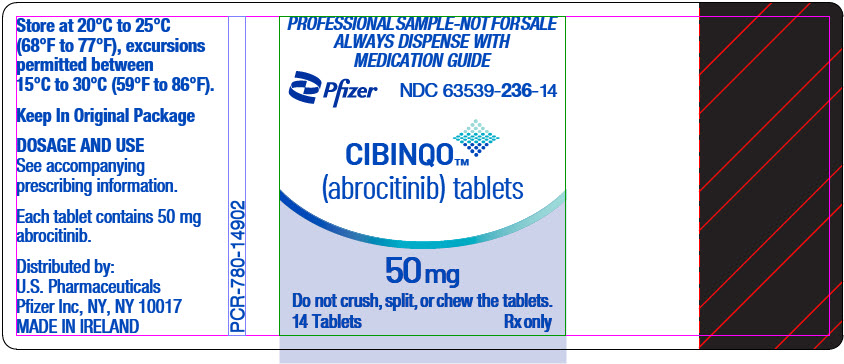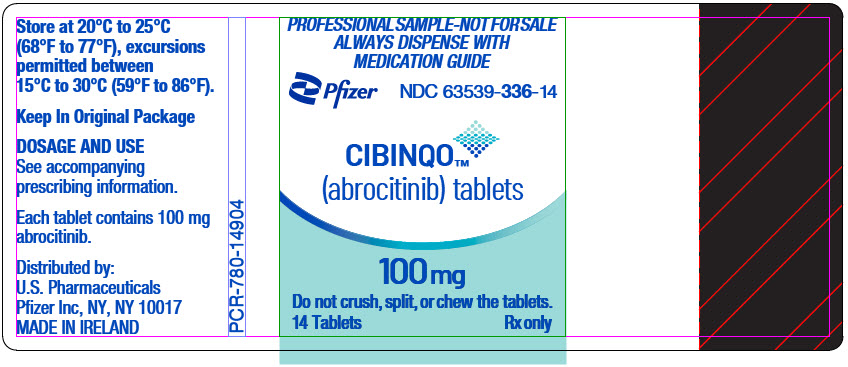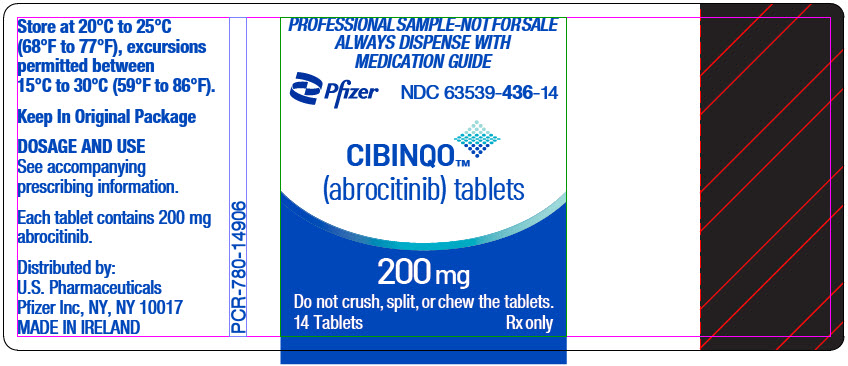 DRUG LABEL: CIBINQO
NDC: 63539-236 | Form: TABLET, FILM COATED
Manufacturer: U.S. Pharmaceuticals
Category: prescription | Type: HUMAN PRESCRIPTION DRUG LABEL
Date: 20250320

ACTIVE INGREDIENTS: ABROCITINIB 50 mg/1 1
INACTIVE INGREDIENTS: MICROCRYSTALLINE CELLULOSE; ANHYDROUS DIBASIC CALCIUM PHOSPHATE; SODIUM STARCH GLYCOLATE TYPE A; MAGNESIUM STEARATE; HYPROMELLOSE, UNSPECIFIED; TITANIUM DIOXIDE; LACTOSE MONOHYDRATE; POLYETHYLENE GLYCOL, UNSPECIFIED; TRIACETIN; FERRIC OXIDE RED

HIGHLIGHTS OF PRESCRIBING INFORMATION

These highlights do not include all the information needed to use CIBINQO safely and effectively. See full prescribing information for CIBINQO.
CIBINQO® (abrocitinib) tablets, for oral use
Initial U.S. Approval: 2022

RECENT MAJOR CHANGES

Indications and Usage (1) | 02/2023
Dosage and Administration (2.2, 2.3, 2.4, 2.5) | 12/2023

WARNING: SERIOUS INFECTIONS, MORTALITY, MALIGNANCY, MAJOR ADVERSE CARDIOVASCULAR EVENTS, and THROMBOSIS

WARNING: SERIOUS INFECTIONS, MORTALITY, MALIGNANCY, MAJOR ADVERSE CARDIOVASCULAR EVENTS (MACE), and THROMBOSIS

See full prescribing information for complete boxed warning.

- Increased risk of serious bacterial, fungal, viral and opportunistic infections leading to hospitalization or death, including tuberculosis (TB). Discontinue treatment with CIBINQO if serious or opportunistic infection occurs. Test for latent TB before and during therapy; treat latent TB prior to use. Monitor all patients for active TB during treatment, even patients with initial negative latent TB test. (5.1)
- Higher rate of all-cause mortality, including sudden cardiovascular death, with another JAK inhibitor vs. TNF blockers in rheumatoid arthritis (RA) patients. CIBINQO is not approved for use in RA patients. (5.2)
- Malignancies have occurred with CIBINQO. Higher rate of lymphomas and lung cancers with another JAK inhibitor vs. TNF blockers in RA patients. (5.3)
- MACE has occurred with CIBINQO. Higher rate of MACE (defined as cardiovascular death, myocardial infarction, and stroke) with another JAK inhibitor vs. TNF blockers in RA patients. (5.4)
- Thrombosis has occurred with CIBINQO. Increased incidence of pulmonary embolism, venous and arterial thrombosis with another JAK inhibitor vs. TNF blockers. (5.5)

1 INDICATIONS AND USAGE

CIBINQO is a Janus kinase (JAK) inhibitor indicated for the treatment of adults and pediatric patients 12 years of age and older with refractory, moderate-to-severe atopic dermatitis whose disease is not adequately controlled with other systemic drug products, including biologics, or when use of those therapies is inadvisable. (1)
Limitation of Use: CIBINQO is not recommended for use in combination with other JAK inhibitors, biologic immunomodulators, or with other immunosuppressants.

2 DOSAGE AND ADMINISTRATION

- For recommended testing, evaluations, and procedures prior to CIBINQO initiation, see Full Prescribing Information. (2.1)
- Recommended dosage is 100 mg orally once daily. (2.2)
- 200 mg orally once daily is recommended for those patients who are not responding to 100 mg once daily. (2.2)
- Moderate renal impairment: 50 mg once daily or 100 mg once daily for those patients who are not responding to 50 mg once daily. (2.3)
- CYP2C19 poor metabolizer: 50 mg once daily or 100 mg once daily for those patients who are not responding to 50 mg once daily. (2.4)
- For dosage modifications for certain adverse reactions, see Full Prescribing Information. (2.6)

3 DOSAGE FORMS AND STRENGTHS

CIBINQO Tablets: 50 mg, 100 mg, and 200 mg (3)

4 CONTRAINDICATIONS

Antiplatelet therapies except for low-dose aspirin (≤81 mg daily), during the first 3 months of treatment. (4)

5 WARNINGS AND PRECAUTIONS

- Laboratory Abnormalities: Laboratory monitoring is recommended due to potential changes in platelets, lymphocytes, and lipids. (5.6)
- Immunizations: Avoid use of live vaccines immediately prior to, during and immediately after CIBINQO treatment. (5.7)

6 ADVERSE REACTIONS

Most common adverse events (≥1% with CIBINQO 100 mg) are nasopharyngitis, nausea, headache, herpes simplex, increased blood creatine phosphokinase, dizziness, urinary tract infection, fatigue, acne, vomiting, impetigo, oropharyngeal pain, hypertension, influenza, gastroenteritis, and dermatitis contact. (6.1)

Most common adverse reactions (≥1% with CIBINQO 200 mg and greater than CIBINQO 100 mg) are nausea, headache, herpes simplex, increased blood creatine kinase, dizziness, urinary tract infection, acne, vomiting, gastroenteritis, upper abdominal pain, abdominal discomfort, herpes zoster, and thrombocytopenia. (6.1)
To report SUSPECTED ADVERSE REACTIONS, contact Pfizer Inc. at 1-800-438-1985 or FDA at 1-800-FDA-1088 or www.fda.gov/medwatch.

7 DRUG INTERACTIONS

- Strong inhibitors of CYP2C19: The recommended dosage is 50 mg once daily or 100 mg once daily for those patients who are not responding to 50 mg once daily. (2.5, 7.1)
- Moderate to strong inhibitors of both CYP2C19 and CYP2C9, or strong CYP2C19 or CYP2C9 inducers: Avoid concomitant use. (7.1)
- P-gp substrate where small concentration changes may lead to serious or life-threatening toxicities: Monitor or titrate dosage of P-gp substrate. (7.2)

8 USE IN SPECIFIC POPULATIONS

- Lactation: Breastfeeding not recommended. (8.2)
- Renal Impairment: Avoid use in patients with severe renal impairment or end-stage renal disease. (8.6)
- Hepatic Impairment: Avoid use in patients with severe hepatic impairment. (8.7)

FULL PRESCRIBING INFORMATION

WARNING: SERIOUS INFECTIONS, MORTALITY, MALIGNANCY, MAJOR ADVERSE CARDIOVASCULAR EVENTS, and THROMBOSIS

Serious Infections

Patients treated with CIBINQO may be at increased risk for developing serious infections that may lead to hospitalization or death. The most frequent serious infections reported with CIBINQO were herpes simplex, herpes zoster, and pneumonia [see Warnings and Precautions (5.1) and Adverse Reactions (6.1)].

If a serious or opportunistic infection develops, discontinue CIBINQO and control the infection.

Reported infections from Janus kinase (JAK) inhibitors used to treat inflammatory conditions:

- Active tuberculosis, which may present with pulmonary or extrapulmonary disease. Test for latent TB before and during therapy; treat latent TB prior to use. Monitor all patients for active TB during treatment, even patients with initial negative latent TB test.
- Invasive fungal infections, including cryptococcosis and pneumocystosis. Patients with invasive fungal infections may present with disseminated, rather than localized, disease.
- Bacterial, viral, including herpes zoster, and other infections due to opportunistic pathogens.

Avoid use of CIBINQO in patients with an active, serious infection including localized infections. The risks and benefits of treatment with CIBINQO should be carefully considered prior to initiating therapy in patients with chronic or recurrent infections.

Patients should be closely monitored for the development of signs and symptoms of infection during and after treatment with CIBINQO, including the possible development of tuberculosis in patients who tested negative for latent tuberculosis infection prior to initiating therapy [see Warnings and Precautions (5.1)].

Mortality

In a large, randomized, postmarketing safety study in rheumatoid arthritis (RA) patients 50 years of age and older with at least one cardiovascular risk factor comparing another JAK inhibitor to TNF blocker treatment, a higher rate of all-cause mortality, including sudden cardiovascular death, was observed with the JAK inhibitor. CIBINQO is not approved for use in RA patients [see Warnings and Precautions (5.2)].

Malignancies

Malignancies were reported in patients treated with CIBINQO. Lymphoma and other malignancies have been observed in patients receiving JAK inhibitors used to treat inflammatory conditions. In RA patients treated with another JAK inhibitor, a higher rate of malignancies (excluding non-melanoma skin cancer (NMSC)) was observed when compared with TNF blockers. Patients who are current or past smokers are at additional increased risk [see Warnings and Precautions (5.3)].

Major Adverse Cardiovascular Events

Major adverse cardiovascular events were reported in patients treated with CIBINQO. In RA patients 50 years of age and older with at least one cardiovascular risk factor treated with another JAK inhibitor, a higher rate of major adverse cardiovascular events (MACE) (defined as cardiovascular death, myocardial infarction, and stroke), was observed when compared with TNF blockers. Patients who are current or past smokers are at additional increased risk. Discontinue CIBINQO in patients that have experienced a myocardial infarction or stroke [see Warnings and Precautions (5.4)].

Thrombosis

Deep venous thrombosis (DVT) and pulmonary embolism (PE) have been reported in patients treated with CIBINQO. Thrombosis, including PE, DVT, and arterial thrombosis have been reported in patients receiving JAK inhibitors used to treat inflammatory conditions. Many of these adverse reactions were serious and some resulted in death. In RA patients 50 years of age and older with at least one cardiovascular risk factor treated with another JAK inhibitor, a higher rate of thrombosis was observed when compared with TNF blockers. Avoid CIBINQO in patients at risk. If symptoms of thrombosis occur, discontinue CIBINQO and treat appropriately [see Warnings and Precautions (5.5)].

1 INDICATIONS AND USAGE

CIBINQO is indicated for the treatment of adults and pediatric patients 12 years of age and older with refractory, moderate-to-severe atopic dermatitis whose disease is not adequately controlled with other systemic drug products, including biologics, or when use of those therapies is inadvisable.

Limitations of Use

CIBINQO is not recommended for use in combination with other JAK inhibitors, biologic immunomodulators, or other immunosuppressants.

2 DOSAGE AND ADMINISTRATION

2.1 Recommended Testing, Evaluations, and Procedures Prior to Treatment Initiation

Perform the following tests and evaluations prior to CIBINQO initiation:

- Tuberculosis (TB) infection evaluation – CIBINQO initiation is not recommended in patients with active TB. For patients with latent TB or those with a negative latent TB test who are at high risk for TB, start preventive therapy for latent TB prior to initiation of CIBINQO [see Warnings and Precautions (5.1)].
- Viral hepatitis screening in accordance with clinical guidelines – CIBINQO initiation is not recommended in patients with active hepatitis B or hepatitis C [see Warnings and Precautions (5.1)].
- A complete blood count (CBC) – CIBINQO initiation is not recommended in patients with a platelet count <150,000/mm^3, an absolute lymphocyte count <500/mm^3, an absolute neutrophil count <1,000/mm^3, or a hemoglobin value <8 g/dL [see Warnings and Precautions (5.6)].

Complete any necessary immunizations, including herpes zoster vaccinations, in agreement with current immunization guidelines prior to CIBINQO initiation [see Warnings and Precautions (5.7)].

2.2 Recommended Dosage

The recommended dose is 100 mg once daily. If an adequate response is not achieved with CIBINQO 100 mg once daily, consider increasing the dosage to 200 mg once daily.

Discontinue CIBINQO if an adequate response is not achieved with 200 mg once daily.

Use the lowest efficacious dose to maintain response.

CIBINQO can be used with or without topical corticosteroids.

If a dose is missed, administer the dose as soon as possible unless it is less than 12 hours before the next dose, in which case skip the missed dose. Thereafter, resume dosing at the regular scheduled time.

2.3 Recommended Dosage in Patients with Renal Impairment or Hepatic Impairment

Renal Impairment

CIBINQO dosage recommendations for patients with renal impairment are provided in Table 1 [see Use in Specific Populations (8.6) and Clinical Pharmacology (12.3)]. In patients with mild and moderate renal impairment, if an adequate response is not achieved with initial dose, the dose of CIBINQO can be doubled [see Dosage and Administration (2.2)].

Table 1. Dosage Recommendations in Patients with Renal Impairment
Renal Impairment Stage | Estimated Glomerular Filtration (eGFR) [Glomerular filtration rate was estimated by the Modification of Diet in Renal Disease (MDRD) formula.] | Dosage
Mild | 60 – 89 mL/minute | CIBINQO 100 mg once daily
Moderate | 30 – 59 mL/minute | CIBINQO 50 mg once daily
Severe [Severe Renal Impairment and End-Stage Renal Disease include patients on renal replacement therapy.] | 15 – 29 mL/minute | Not recommended for use
End-Stage Renal Disease (ESRD) | <15 mL/minute | Not recommended for use

Hepatic Impairment

CIBINQO is not recommended for use in patients with severe hepatic impairment [see Use in Specific Populations (8.7) and Clinical Pharmacology (12.3)].

2.4 Recommended Dosage in CYP2C19 Poor Metabolizers

In patients who are known or suspected to be CYP2C19 poor metabolizers, the recommended dosage of CIBINQO is 50 mg once daily [see Use in Specific Populations (8.8) and Clinical Pharmacology (12.5)]. If an adequate response is not achieved with CIBINQO 50 mg once daily, consider increasing the dosage to 100 mg once daily. Discontinue therapy if inadequate response is seen after dosage increase to 100 mg once daily.

2.5 Dosage Modifications due to Strong Inhibitors

In patients taking strong inhibitors of cytochrome P450 (CYP) 2C19, reduce the dosage to 50 mg once daily [see Drug Interactions (7.1) and Clinical Pharmacology (12.3)]. If an adequate response is not achieved with CIBINQO 50 mg daily, consider increasing the dosage to 100 mg once daily. Discontinue therapy if inadequate response is seen after dosage increase to 100 mg once daily.

2.6 Treatment Discontinuation due to Serious Infections or Hematologic Adverse Reactions

Serious or Opportunistic Infections

If a patient develops a serious or opportunistic infection, discontinue CIBINQO and control the infection. The risks and benefits of treatment with CIBINQO should be carefully considered prior to reinitiating therapy with CIBINQO [see Warnings and Precautions (5.1)].

Hematologic Abnormalities

Recommendations for CIBINQO discontinuation for laboratory abnormalities are summarized in Table 2.

Table 2. Recommendations for CIBINQO Discontinuation for Hematologic Abnormalities
Laboratory Measure | Recommendation
Platelet Count <50,000/mm^3 | Discontinue CIBINQO and follow with CBC until >100,000/mm^3
ALC <500/mm^3 | Treatment should be temporarily discontinued if ALC is less than 500 cells/mm^3 and may be restarted once ALC return above this value
ANC <1,000/mm^3 | Treatment should be temporarily discontinued if ANC is less than 1,000 cells/mm^3 and may be restarted once ANC return above this value
Hb value <8 g/dL | Treatment should be temporarily discontinued if Hb is less than 8 g/dL and may be restarted once Hb return above this value
Abbreviations: ALC=absolute lymphocyte count; ANC=absolute neutrophil count; CBC=complete blood count; Hb=hemoglobin

CBC evaluations are recommended at baseline, 4 weeks after treatment initiation and 4 weeks after dosage increase of CIBINQO. Laboratory evaluations may be extended for patients on chronic CIBINQO therapy who develop hematologic abnormalities [see Warnings and Precautions (5.6)].

2.7 Administration Instructions

Administer CIBINQO with or without food at approximately the same time each day.

Swallow CIBINQO tablets whole with water. Do not crush, split, or chew CIBINQO tablets.

3 DOSAGE FORMS AND STRENGTHS

- 50 mg: Pink, oval, film-coated tablet debossed with "PFE" on one side and "ABR 50" on the other.
- 100 mg: Pink, round, film-coated tablet debossed with "PFE" on one side and "ABR 100" on the other.
- 200 mg: Pink, oval, film-coated tablet debossed with "PFE" on one side and "ABR 200" on the other.

4 CONTRAINDICATIONS

CIBINQO is contraindicated in patients taking antiplatelet therapies, except for low-dose aspirin (≤81 mg daily), during the first 3 months of treatment [see Warnings and Precautions (5.6), Drug Interactions (7.2), and Clinical Pharmacology (12.2)].

5 WARNINGS AND PRECAUTIONS

5.1 Serious Infections

The most frequent serious infections reported in clinical studies with CIBINQO for atopic dermatitis were herpes simplex, herpes zoster, and pneumonia [see Adverse Reactions (6.1)]. Serious infections leading to hospitalization or death, including tuberculosis and bacterial, invasive fungal, viral, and other opportunistic infections, have occurred in patients receiving JAK inhibitors used to treat inflammatory conditions.

Avoid use of CIBINQO in patients with active, serious infection including localized infections.

Consider the risks and benefits of treatment prior to initiating CIBINQO in patients:

- with chronic or recurrent infection
- who have been exposed to tuberculosis
- with a history of a serious or an opportunistic infection
- who have resided or traveled in areas of endemic tuberculosis or endemic mycoses
- with underlying conditions that may predispose them to infection

Closely monitor patients for the development of signs and symptoms of infection during and after treatment with CIBINQO. If a patient develops a serious or opportunistic infection, discontinue CIBINQO. Initiate complete diagnostic testing and appropriate antimicrobial therapy. The risks and benefits of treatment with CIBINQO should be carefully considered prior to reinitiating therapy with CIBINQO.

Tuberculosis

Evaluate and test patients for TB before starting CIBINQO therapy and consider yearly screening for patients in highly endemic areas for TB. CIBINQO is not recommended for use in patients with active TB. For patients with a new diagnosis of latent TB or prior untreated latent TB, or for patients with a negative test for latent TB but who are at high risk for TB infection, start preventive therapy for latent TB prior to initiation of CIBINQO. Monitor patients for the development of signs and symptoms of TB, including patients who were tested negative for latent TB infection prior to initiating therapy.

Viral Reactivation

Viral reactivation, including herpes virus reactivation (e.g., herpes zoster, herpes simplex), was reported in clinical trials with CIBINQO [see Adverse Reactions (6.1)]. If a patient develops herpes zoster, consider interrupting CIBINQO until the episode resolves.

Hepatitis B virus (HBV) reactivation has been reported in patients receiving JAK inhibitors. Perform viral hepatitis screening in accordance with clinical guidelines before starting therapy and monitor for reactivation during therapy with CIBINQO. CIBINQO is not recommended for use in patients with active hepatitis B or hepatitis C [see Clinical Pharmacology (12.3)]. Monitor patients with inactive HBV for expression of HBV DNA during therapy with CIBINQO. If HBV DNA is detected during therapy with CIBINQO, consult a liver specialist.

5.2 Mortality

In a large, randomized, postmarketing safety trial of another JAK inhibitor in rheumatoid arthritis (RA) patients 50 years of age and older with at least one cardiovascular risk factor, a higher rate of all-cause mortality, including sudden cardiovascular death, was observed in subjects treated with the JAK inhibitor compared with TNF blockers. CIBINQO is not approved for use in RA.

Consider the benefits and risks for the individual patient prior to initiating or continuing therapy with CIBINQO.

5.3 Malignancy and Lymphoproliferative Disorders

Malignancies, including non-melanoma skin cancer (NMSC), were observed in clinical trials with CIBINQO for atopic dermatitis [see Adverse Reactions (6.1)].

Perform periodic skin examination for patients who are at increased risk for skin cancer. Exposure to sunlight and UV light should be limited by wearing protective clothing and using broad-spectrum sunscreen.

Malignancies, including lymphomas, have occurred in patients receiving JAK inhibitors used to treat inflammatory conditions. In a large, randomized, postmarketing safety trial of another JAK inhibitor in RA subjects, a higher rate of malignancies (excluding non-melanoma skin cancer (NMSC)) was observed in subjects treated with the JAK inhibitor compared to those treated with TNF blockers. CIBINQO is not approved for use in RA. A higher rate of lymphomas was observed in subjects treated with the JAK inhibitor compared to those treated with TNF blockers. A higher rate of lung cancers was observed in current or past smokers treated with the JAK inhibitor compared to those treated with TNF blockers. In this trial, current or past smokers had an additional increased risk of overall malignancies.

Consider the benefits and risks for the individual patient prior to initiating or continuing therapy with CIBINQO, particularly in patients with a known malignancy (other than a successfully treated NMSC), patients who develop a malignancy when on treatment, and patients who are current or past smokers.

5.4 Major Adverse Cardiovascular Events

Major adverse cardiovascular events were reported in clinical trials of CIBINQO for atopic dermatitis [see Adverse Reactions (6.1)].

In a large, randomized, postmarketing safety trial of another JAK inhibitor in RA subjects 50 years of age and older with at least one cardiovascular risk factor, a higher rate of major adverse cardiovascular events (MACE) defined as cardiovascular death, non-fatal myocardial infarction (MI), and non-fatal stroke was observed with the JAK inhibitor compared to those treated with TNF blockers. CIBINQO is not approved for use in RA. Patients who are current or past smokers are at additional increased risk.

Consider the benefits and risks for the individual patient prior to initiating or continuing therapy with CIBINQO, particularly in patients who are current or past smokers and patients with other cardiovascular risk factors. Patients should be informed about the symptoms of serious cardiovascular events and the steps to take if they occur. Discontinue CIBINQO in patients that have experienced a myocardial infarction or stroke.

5.5 Thrombosis

Deep venous thrombosis (DVT) and pulmonary embolism (PE) were observed in subjects receiving CIBINQO in the clinical trials for atopic dermatitis [see Adverse Reactions (6.1)].

Thrombosis, including DVT, PE, and arterial thrombosis have been reported in patients receiving JAK inhibitors used to treat inflammatory conditions. Many of these adverse reactions were serious and some resulted in death.

In a large, randomized, postmarketing safety trial of another JAK inhibitor in RA subjects 50 years of age and older with at least one cardiovascular risk factor, higher rates of overall thrombosis, DVT, and PE were observed compared to those treated with TNF blockers. CIBINQO is not approved for use in RA.

Avoid CIBINQO in patients that may be at increased risk of thrombosis. If symptoms of thrombosis occur, discontinue CIBINQO and evaluate and treat patients appropriately.

5.6 Laboratory Abnormalities

Hematologic Abnormalities

Treatment with CIBINQO was associated with an increased incidence of thrombocytopenia and lymphopenia [see Adverse Reactions (6.1)]. Prior to CIBINQO initiation, perform a CBC [see Dosage and Administration (2.1)]. CBC evaluations are recommended at 4 weeks after initiation and 4 weeks after dose increase of CIBINQO. Discontinuation of CIBINQO therapy is required for certain laboratory abnormalities [see Dosage and Administration (2.6)].

Lipid Elevations

Dose-dependent increase in blood lipid parameters were reported in subjects treated with CIBINQO [see Adverse Reactions (6.1)]. Lipid parameters should be assessed approximately 4 weeks following initiation of CIBINQO therapy and thereafter patients should be managed according to clinical guidelines for hyperlipidemia. The effect of these lipid parameter elevations on cardiovascular morbidity and mortality has not been determined.

5.7 Immunizations

Prior to initiating CIBINQO, complete all age-appropriate vaccinations as recommended by current immunization guidelines, including prophylactic herpes zoster vaccinations. Avoid vaccination with live vaccines immediately prior to, during and immediately after CIBINQO therapy.

6 ADVERSE REACTIONS

The following clinically significant adverse reactions are described elsewhere in the labeling:

- Serious Infections [see Warnings and Precautions (5.1)]
- Mortality [see Warnings and Precautions (5.2)]
- Malignancy and Lymphoproliferative Disorders [see Warnings and Precautions (5.3)]
- Major Adverse Cardiovascular Events [see Warnings and Precautions (5.4)]
- Thrombosis [see Warnings and Precautions (5.5)]
- Laboratory Abnormalities [see Warnings and Precautions (5.6)]

6.1 Clinical Trials Experience

Because clinical trials are conducted under widely varying conditions, adverse reaction rates observed in the clinical trials of a drug cannot be directly compared to rates in the clinical trials of another drug and may not reflect the rates observed in practice.

The safety of CIBINQO was evaluated in four randomized, placebo-controlled clinical trials (2 monotherapy, 1 combination therapy with topical corticosteroid, and 1 dose-ranging) and one long-term extension trial in subjects with moderate to severe atopic dermatitis (AD). A total of 1623 subjects with moderate to severe atopic dermatitis were treated with CIBINQO in these clinical trials representing 1428 patient-years of exposure. There were 634 subjects with at least 1 year of exposure to CIBINQO.

In the placebo-controlled clinical trials, a total of 1198 subjects were exposed to CIBINQO with 608 subjects receiving CIBINQO 100 mg once daily and 590 subjects receiving CIBINQO 200 mg once daily for up to 16 weeks. The median age of subjects was 33.0 years, 124 subjects (8.1%) were 12 to less than 18 years old and 94 subjects (6.1%) were 65 years of age or older. The majority of subjects were White (68.7%) and male (53.9%).

Adverse reactions occurring at ≥1% in any of the treated groups and at a higher rate than in the placebo group are presented in Table 3. A total of 61 (5.1%) subjects treated with CIBINQO were discontinued from the trials due to adverse reactions. The safety profile of CIBINQO in the monotherapy and the combination trial(s) were similar.

Table 3. Adverse Reactions from Placebo-Controlled Trials Reported in ≥1% of CIBINQO Treated Subjects with Moderate to Severe Atopic Dermatitis and at Higher Rate than Placebo for up to 16 Weeks
 | Weeks 0–16
 | CIBINQO 200 mg N=590 n (% [Study size adjusted percentages]) | CIBINQO 100 mg N=608 n (%) | Placebo N=342 n (%)
Nasopharyngitis | 51 (8.7) | 75 (12.4) | 27 (7.9)
Nausea | 86 (14.5) | 37 (6.0) | 7 (2.1)
Headache | 46 (7.8) | 36 (6.0) | 12 (3.5)
Herpes simplex [Herpes simplex also includes oral herpes, ophthalmic herpes, herpes dermatitis, genital herpes.] | 25 (4.2) | 20 (3.3) | 6 (1.8)
Increased blood creatine phosphokinase | 17 (2.9) | 14 (2.3) | 5 (1.5)
Dizziness | 17 (2.9) | 11 (1.8) | 3 (0.9)
Urinary tract infection | 13 (2.2) | 10 (1.7) | 4 (1.2)
Fatigue | 8 (1.3) | 10 (1.6) | 2 (0.5)
Acne | 28 (4.7) | 10 (1.6) | 0 (0.0)
Vomiting | 19 (3.2) | 9 (1.5) | 3 (0.9)
Impetigo | 3 (0.5) | 9 (1.5) | 1 (0.3)
Oropharyngeal pain | 6 (1.0) | 8 (1.4) | 2 (0.6)
Hypertension | 5 (0.8) | 7 (1.2) | 2 (0.7)
Influenza | 6 (1.1) | 7 (1.2) | 0 (0.0)
Gastroenteritis | 8 (1.3) | 7 (1.1) | 2 (0.6)
Dermatitis contact | 3 (0.5) | 6 (1.1) | 1 (0.3)
Abdominal pain upper | 11 (1.9) | 4 (0.6) | 0 (0.0)
Abdominal discomfort | 7 (1.2) | 3 (0.5) | 1 (0.3)
Herpes zoster | 7 (1.2) | 2 (0.3) | 0 (0.0)
Thrombocytopenia | 9 (1.5) | 0 (0.0) | 0 (0.0)

Specific Adverse Reactions

Exposure adjusted incidence rates were adjusted by trial size for all the adverse reactions reported in this section.

Overall Infections

In the placebo-controlled trials, for up to 16 weeks, overall infections were reported in 90 subjects (126.8 per 100 patient-years) treated with placebo, 211 subjects (168.8 per 100 patient-years) treated with CIBINQO 100 mg and 204 subjects (159.5 per 100 patient-years) treated with CIBINQO 200 mg. In all 5 clinical trials, including the long-term extension trial, overall infections were reported in 427 subjects (91.8 per 100 patient-years) treated with CIBINQO 100 mg and 394 subjects (103.2 per 100 patient-years) treated with CIBINQO 200 mg.

Serious Infections

In the placebo-controlled trials, for up to 16 weeks, serious infections were reported in 2 subjects (2.6 per 100 patient-years) treated with placebo, 6 subjects (3.9 per 100 patient-years) treated with CIBINQO 100 mg, and 2 subjects (1.3 per 100 patient-years) treated with CIBINQO 200 mg. In all 5 clinical trials, including the long-term extension trial, serious infections were reported in 18 subjects (2.3 per 100 patient-years) treated with CIBINQO 100 mg and 16 subjects (2.3 per 100 patient-years) treated with CIBINQO 200 mg. The most commonly reported serious infections were herpes simplex, herpes zoster, and pneumonia.

Herpes Zoster

In the placebo-controlled trials, for up to 16 weeks, opportunistic infections were generally cases of multidermatomal cutaneous herpes zoster. Herpes zoster was reported in 0 subjects treated with placebo, 3 subjects (1.9 per 100 patient-years) treated with CIBINQO 100 mg and 8 subjects (5.1 per 100 patient-years) treated with CIBINQO 200 mg. In all 5 clinical trials, including the long-term extension trial, herpes zoster was reported in 16 subjects (2.0 per 100 patient-years) treated with CIBINQO 100 mg and 35 subjects (5.2 per 100 patient-years) treated with CIBINQO 200 mg.

Malignancy

In the placebo-controlled trials, for up to 16 weeks, no malignancy was reported in subjects treated with placebo or CIBINQO 100 mg and in 1 patient (0.65 per 100 patient-years) treated with CIBINQO 200 mg. In all 5 clinical trials, including the long-term extension trial, malignancy was reported in 4 subjects (0.5 per 100 patient-years) treated with CIBINQO 100 mg and 2 subjects (0.3 per 100 patient-years) treated with CIBINQO 200 mg.

Thrombosis

In all clinical trials, including the long-term extension trial, pulmonary embolism was reported in 3 subjects (0.4 per 100 patient-years), who were treated with CIBINQO 200 mg. Deep vein thrombosis was reported in 2 subjects (0.3 per 100 patient-years) who were treated with CIBINQO 200 mg. No thrombosis occurred in subjects treated with CIBINQO 100 mg.

Major Adverse Cardiovascular Events

In the placebo-controlled trials, for up to 16 weeks, major adverse cardiovascular event (MACE) was reported in 1 subject (0.6 per 100 patient-years) treated with CIBINQO 100 mg. In all 5 clinical trials, including the long-term extension trial, MACE was reported in 1 patient (0.1 per 100 patient-years) treated with CIBINQO 100 mg and 2 subjects (0.3 per 100 patient-years) treated with CIBINQO 200 mg.

Thrombocytopenia

In the placebo-controlled trials, for up to 16 weeks, treatment with CIBINQO was associated with a dose-related decrease in platelet count. Maximum effects on platelets were observed within 4 weeks, after which the platelet count returned towards baseline despite continued therapy. In all 5 clinical trials, including the long-term extension trial, 6 subjects (0.9 per 100 patient-years) treated with CIBINQO 200 mg had adverse reactions of thrombocytopenia; no subjects treated with CIBINQO 100 mg had an adverse reaction of thrombocytopenia.

Lymphopenia

In the placebo-controlled trials, for up to 16 weeks, confirmed ALC <500/mm^3 occurred in 2 subjects (1.2 per 100 patient-years) treated with CIBINQO 200 mg and 0 subjects treated with CIBINQO 100 mg or placebo. Both cases occurred in the first 4 weeks of exposure.

Lipid Elevations

In the placebo-controlled trials, for up to 16 weeks, there was a dose-related percent increase in low-density lipoprotein cholesterol (LDL-c), total cholesterol, and high-density lipoprotein cholesterol (HDL-c) relative to placebo at Week 4 which remained elevated through the final visit in the treatment period. Adverse reactions related to hyperlipidemia occurred in 1 subject (0.6 per 100 patient-years) exposed to CIBINQO 100 mg, 3 subjects (2.0 per 100 patient-years) exposed to CIBINQO 200 mg.

Retinal Detachment

In the placebo-controlled trials, for up to 16 weeks, retinal detachment occurred in 1 subject (0.6 per 100 patient-years) treated with CIBINQO 100 mg. In all 5 clinical trials, including the long-term extension trial, retinal detachment occurred in 2 subjects (0.3 per 100 patient-years) treated with CIBINQO 100 mg.

Creatine Phosphokinase Elevations (CPK)

In the placebo-controlled trials, for up to 16 weeks, events of blood CPK increased were reported in 6 subjects (7.5 per 100 patient-years) treated with placebo, 11 subjects (6.9 per 100 patient-years) treated with 100 mg of CIBINQO and 19 subjects (12.3 per 100 patient-years) treated with 200 mg of CIBINQO. Most elevations were transient, there were no reported adverse reactions of rhabdomyolysis.

Pediatric Subjects (12 to less than 18 years of age)

The safety of CIBINQO was assessed in a trial of 284 subjects 12 to less than 18 years of age with moderate-to-severe atopic dermatitis (Trial-AD-4). The safety profile of CIBINQO in these subjects, assessed through the initial treatment period of 12 weeks and the long-term period (213 with at least 52 weeks of abrocitinib exposure), was comparable to the safety profile from trials in adults with atopic dermatitis.

7 DRUG INTERACTIONS

7.1 Effects of Other Drugs on CIBINQO

Table 4 includes drugs with clinically significant drug interactions affecting CIBINQO.

Table 4. Clinically Significant Drug Interactions Affecting CIBINQO
Strong CYP2C19 Inhibitors
Clinical Impact | Coadministration of CIBINQO with strong CYP2C19 inhibitors increases the combined exposure of abrocitinib and its two active metabolites, M1 and M2 which may increase the adverse reactions of CIBINQO [see Clinical Pharmacology (12.3)].
Intervention | Dosage reduction of CIBINQO is recommended when coadministered with strong CYP2C19 inhibitors [see Dosage and Administration (2.5)].
Moderate to Strong Inhibitors of both CYP2C19 and CYP2C9
Clinical Impact | Coadministration of CIBINQO with drugs that are moderate to strong inhibitors of both CYP2C19 and CYP2C9 increases the exposure of abrocitinib and its two active metabolites, M1 and M2 which may increase the adverse reactions of CIBINQO [Clinical Pharmacology (12.3)].
Intervention | Avoid concomitant use of CIBINQO with drugs that are moderate to strong inhibitors of both CYP2C19 and CYP2C9.
Strong CYP2C19 or CYP2C9 Inducers
Clinical Impact | Coadministration of CIBINQO with strong CYP2C19 or CYP2C9 inducers decreases the combined exposure of abrocitinib and its two active metabolites, M1 and M2, which may result in loss of or reduced clinical response [see Clinical Pharmacology (12.3)].
Intervention | Avoid concomitant use of CIBINQO with strong CYP2C19 or CYP2C9 inducers.

7.2 Effects of CIBINQO on Other Drugs

Table 5 includes clinically significant drug interactions affecting other drugs.

Table 5. Clinically Significant Interactions Affecting Other Drugs
P-gp Substrate Where Small Concentration Changes May Lead to Serious or Life-threatening Toxicities
Clinical Impact | Coadministration of CIBINQO with P-gp substrate increases plasma concentrations of P-gp substrates and may result in potential adverse reactions of the P-gp substrate where small concentration changes may lead to serious or life-threatening toxicities (e.g., digoxin) [see Clinical Pharmacology (12.3)].
Intervention | Monitor appropriately or dose titrate P-gp substrate where small concentration changes may lead to serious or life-threatening toxicities when coadministered with CIBINQO.
Antiplatelet Therapy Drugs
Clinical Impact | Coadministration of CIBINQO with antiplatelet therapy drugs may increase the risk of bleeding with thrombocytopenia [see Warnings and Precautions (5.5) and Clinical Pharmacology (12.2)].
Intervention | Antiplatelet drugs, except for low-dose aspirin (≤81 mg daily), during the first 3 months of treatment are contraindicated with CIBINQO [see Contraindications (4)].

8 USE IN SPECIFIC POPULATIONS

8.1 Pregnancy

Pregnancy Exposure Registry

There is a pregnancy exposure registry that monitors pregnancy outcomes in women exposed to CIBINQO during pregnancy. Pregnant women exposed to CIBINQO and health care providers are encouraged to call 1-877-311-3770.

Risk Summary

Available data from pregnancies reported in clinical trials with CIBINQO are not sufficient to establish a drug‑associated risk for major birth defects, miscarriage, or other adverse maternal or fetal outcomes. In animal reproduction studies, oral administration of abrocitinib to pregnant rats and rabbits during organogenesis at exposure 11 or 4 times the maximum recommended human dose (MRHD) based on AUC comparison, respectively, resulted in maternal dystocia and skeletal variations in rats and no adverse effects in rabbits (see Data).

The background risks of major birth defects and miscarriage for the indicated population are unknown. All pregnancies carry some risk of birth defects, loss, or other adverse outcomes. The background risks in the U.S. general population of major birth defects and miscarriages are 2–4% and 15–20% of clinically recognized pregnancies, respectively.

Data

Animal Data

In an embryofetal development study, abrocitinib was administered orally to pregnant rats at doses of 10, 30, or 60 mg/kg/day during the period of organogenesis. No fetal malformations were observed. Abrocitinib increased the incidence of skeletal variations of short 13th ribs at 30 mg/kg/day (11 times the MRHD based on AUC comparison). Increased embryofetal lethality and additional skeletal variations (cervical arches with reduced ventral processes, thickened ribs, and unossified metatarsals) were noted at 60 mg/kg/day (17 times the MRHD based on AUC comparison).

In an embryofetal development study, abrocitinib was administered orally to pregnant rabbits at doses of 10, 30, or 75 mg/kg/day during the period of organogenesis. No abrocitinib-related maternal or developmental toxicity was noted at doses up to 75 mg/kg/day (4 times the MRHD based on AUC comparison).

In a prenatal and postnatal development study, abrocitinib was administered orally to pregnant rats at doses of 10, 30, and 60 mg/kg/day beginning on gestation day 6 and continuing through lactation day 20. Dystocia with prolonged parturition and reduced offspring body weights were noted at 30 mg/kg/day (11 times the MRHD based on AUC comparison). Postnatal survival was markedly decreased at 60 mg/kg/day (17 times the MRHD based on AUC comparison). No maternal toxicity was observed at 10 mg/kg/day (2.4 times the MRHD based on AUC comparison). No abrocitinib-related effects on postnatal developmental, neurobehavioral, or reproductive performance of offspring was noted at doses up to 30 mg/kg/day (11 times the MRHD based on AUC comparison).

8.2 Lactation

Risk Summary

There are no data on the presence of abrocitinib in human milk, the effects on the breast-fed infant, or the effects on milk production. Abrocitinib was secreted in milk of lactating rats (see Data). When a drug is present in animal milk, it is likely that the drug will be present in human milk. Because of the serious adverse findings in adults, including risks of serious infections, malignancy, and thrombosis, advise women not to breastfeed during treatment with CIBINQO and for one day after the last dose (approximately 5–6 elimination half-lives).

Data

Animal Data

Lactating female rats were orally administered a single dose of 10 mg/kg abrocitinib on lactation day 12. Abrocitinib AUC was approximately 5 times greater in milk than in plasma.

8.3 Females and Males of Reproductive Potential

Infertility

Females

Based on the findings in rats, oral administration of CIBINQO may impair female fertility. Impaired fertility in female rats was reversible 1 month after cessation of abrocitinib oral administration [see Nonclinical Toxicology (13.1)].

8.4 Pediatric Use

The safety and effectiveness of CIBINQO in pediatric patients 12 years of age and older with atopic dermatitis have been established.

In trials Trial-AD-1 and Trial-AD-2, 124 pediatric subjects 12 to less than 18 years old weighing 25 kg or more with moderate-to-severe atopic dermatitis were enrolled and randomized to receive either CIBINQO 100 mg (N=51), 200 mg (N=48), or matching placebo (N=25) in monotherapy. Additional 284 pediatric subjects 12 to less than 18 years of age weighing 25 kg or more with moderate-to-severe atopic dermatitis, were enrolled and randomized to receive either CIBINQO 100 mg (N=95) or 200 mg (N=94) or matching placebo (N=95) in combination with topical corticosteroids in Trial-AD-4. Efficacy and adverse reaction profile were comparable between the pediatric patients and adults [see Clinical Studies (14) and Adverse Reactions (6.1)].

The safety and effectiveness of CIBINQO have not been established in pediatric patients below 12 years of age.

Juvenile Animal Toxicity Data

In a juvenile animal toxicity study, abrocitinib was administered orally to juvenile rats at doses of 5, 25, and 75 mg/kg/day from postnatal day 10 (approximately equivalent to a human infant) through postnatal day 63 (approximately equivalent to an adolescent). Abrocitinib caused a reversible, dose‑related decrease in the primary spongiosa in the metaphysis of the proximal tibia and distal femur and adverse effects on bone development at all dose levels. Abrocitinib caused irreversible dose-related small or misshapen femoral heads at doses ≥5 mg/kg/day (0.8 times the MRHD based on AUC comparison); irreversibly decreased femur size and caused paw malrotation and limb impairment at doses ≥25 mg/kg/day (7.2 times the MRHD based on AUC comparison); and fractures at 75 mg/kg/day (27 times the MRHD based on AUC comparison).

In a follow-up study, abrocitinib (25 mg/kg/day, at least 4.5 times the MRHD based on AUC comparison) was orally administered to juvenile rats from postnatal day (PND) 10, 15, 21, or 30 through PND day 63. Administration beginning PND 10 caused adverse macroscopic and microscopic bone findings consistent with the previous juvenile animal study. However, administration beginning PND 15 (approximately equivalent to a 6- to 12-month old infant) caused non-adverse reversible microscopic bone findings. No bone findings were noted when administration began on PND 21 or 30 (approximately equivalent to 2- and 6-year old children, respectively).

8.5 Geriatric Use

A total of 145 (4.6%) subjects 65 years of age and older, while 25 (0.8%) were 75 years of age and older, were enrolled in CIBINQO clinical trials. Clinical trials of CIBINQO did not include sufficient numbers of subjects 65 years of age and older to determine whether they respond differently from younger adult subjects.

A higher proportion of subjects 65 years of age and older discontinued from clinical trials compared to younger subjects. Among all subjects exposed to CIBINQO, including the long-term extension trial, confirmed ALC <500/mm^3 occurred only in subjects 65 years of age and older. A higher proportion of subjects 65 years of age and older had platelet counts <75,000/mm^3. The incidence rate of herpes zoster in subjects 65 years of age and older treated with CIBINQO (7.40 per 100 patient-years) was higher than that of subjects 18 to less than 65 years of age (3.44 per 100 patient-years).

8.6 Renal Impairment

In patients with severe (eGFR <30 mL/min) and moderate (eGFR 30–59 mL/min) renal impairment, the combined exposure (AUCinf,u) of abrocitinib and its two active metabolites, M1 and M2, is increased compared to patients with normal renal function (eGFR ≥90 mL/min) [see Clinical Pharmacology (12.3)]. This may increase the risk of adverse reactions such as infections.

CIBINQO is not recommended for use in patients with severe renal impairment and ESRD including those on renal replacement therapy [see Dosage and Administration (2.3)].

A dosage reduction in patients with moderate renal impairment is recommended. No dosage adjustment is required in patients with mild renal impairment (eGFR 60–89 mL/min) [see Dosage and Administration (2.3)].

CIBINQO has not been studied in subjects on renal replacement therapy. In Phase 3 clinical trials, CIBINQO was not evaluated in subjects with atopic dermatitis with baseline creatinine clearance values less than 40 mL/min.

8.7 Hepatic Impairment

Avoid use of CIBINQO in patients with severe (Child Pugh C) hepatic impairment. In clinical trials, CIBINQO was not evaluated in subjects with severe (Child Pugh C) hepatic impairment.

Dosage adjustment is not required in patients with mild (Child Pugh A) or moderate (Child Pugh B) hepatic impairment based on similar combined exposure (AUCinf,u) of abrocitinib and its two active metabolites, M1 and M2 compared to patients with normal hepatic function [see Clinical Pharmacology (12.3)].

8.8 CYP2C19 Poor Metabolizers

In patients who are CYP2C19 poor metabolizers, the AUC of abrocitinib is increased compared to CYP2C19 normal metabolizers due to reduced metabolic clearance. Dosage reduction of CIBINQO is recommended in patients who are known or suspected to be CYP2C19 poor metabolizers based on genotype or previous history/experience with other CYP2C19 substrates [see Dosage and Administration (2.4) and Clinical Pharmacology (12.5)].

10 OVERDOSAGE

There is no experience regarding human overdosage with CIBINQO. There is no specific antidote for overdose with CIBINQO. In case of an overdose, call Poison Control Center at 1-800-222-1222 for latest recommendations.

11 DESCRIPTION

CIBINQO (abrocitinib) tablets contain the free base of abrocitinib, a Janus kinase (JAK) inhibitor, for oral administration.

Abrocitinib is a white to pale colored powder with the following chemical name: N-((1s,3s)-3-(methyl(7H-pyrrolo[2,3-d]pyrimidin-4-yl)amino)cyclobutyl)propane-1-sulfonamide

The solubility of abrocitinib in water is 0.04 mg/mL at 25ºC.

Abrocitinib has a molecular weight of 323.42 g/mol and a molecular formula of C14H21N5O2S. The structural formula of abrocitinib is:

Each film-coated tablet contains 50 mg or 100 mg or 200 mg of abrocitinib and the following inactive ingredients: dibasic calcium phosphate anhydrous, hypromellose, iron oxide red, lactose monohydrate, Macrogol, magnesium stearate, microcrystalline cellulose, sodium starch glycolate, titanium dioxide, and triacetin.

12 CLINICAL PHARMACOLOGY

12.1 Mechanism of Action

CIBINQO is a Janus kinase (JAK) inhibitor.

Abrocitinib reversibly inhibits JAK1 by blocking the adenosine triphosphate (ATP) binding site. In a cell-free isolated enzyme assay, abrocitinib was selective for JAK1 over JAK2 (28-fold), JAK3 (>340-fold), and tyrosine kinase (TYK) 2 (43-fold), as well as the broader kinome. The relevance of inhibition of specific JAK enzymes to therapeutic effectiveness is not currently known. Both the parent compound and the active metabolites inhibit JAK1 activity in vitro with similar levels of selectivity.

12.2 Pharmacodynamics

Treatment with CIBINQO was associated with dose-dependent reduction in serum markers of inflammation, including high sensitivity C-reactive protein (hsCRP), interleukin-31 (IL-31) and thymus and activation regulated chemokine (TARC). These changes returned to near baseline within 4 weeks of drug discontinuation.

Effect on Platelet Count

Treatment with CIBINQO was also associated with a transient, dose-dependent decrease in platelet count with the nadir occurring at a median of 24 days after continuous administration of abrocitinib 200 mg once daily. The percent change from baseline of the nadir increases with decreasing baseline platelet counts (-41.2%, -33.4%, and -26.5% for baseline platelet counts of 170, 220, and 270 × 10^3/mm^3, respectively). Partial recovery of platelet count (~40% recovery in platelet count by 12 weeks) occurred without discontinuation of the treatment.

Cardiac Electrophysiology

At a dose 3 times the maximum approved recommended dose, abrocitinib does not prolong the QT interval to any clinically relevant extent.

12.3 Pharmacokinetics

Abrocitinib plasma Cmax and AUC increased dose proportionally up to 200 mg. Steady-state plasma concentrations of abrocitinib are achieved within 48 hours after once daily administration.

Absorption

Abrocitinib is absorbed with over 91% extent of oral absorption and absolute oral bioavailability of approximately 60%. The peak plasma concentrations of abrocitinib are reached within 1 hour.

Effect of Food

Coadministration of CIBINQO with a high-fat, high-calorie meal (total 916 calories, with approximate distribution of 55% fat, 29% carbohydrates, and 16% protein) had no clinically relevant effect on abrocitinib exposures (AUC and Cmax of abrocitinib increased by approximately 26% and 29%, respectively, and Tmax was prolonged by 2 hours) [see Dosage and Administration (2.7)].

Distribution

After intravenous administration, the volume of distribution of abrocitinib is approximately 100 L. Approximately 64%, 37% and 29% of circulating abrocitinib and its active metabolites M1 and M2, respectively, are bound to plasma proteins. Abrocitinib and its active metabolites M1 and M2 bind predominantly to albumin and distribute equally between red blood cells and plasma.

Elimination

Abrocitinib is eliminated primarily by metabolic clearance mechanisms. The mean elimination half-lives of abrocitinib and its two active metabolites, M1 and M2, range 3 to 5 hours.

Metabolism

The metabolism of abrocitinib is mediated by multiple CYP enzymes, CYP2C19 (~53%), CYP2C9 (~30%), CYP3A4 (~11%) and CYP2B6 (~6%). In a human radiolabeled study, abrocitinib was the most prevalent circulating species, with two active polar mono-hydroxylated metabolites identified as M1 (3-hydroxypropyl), and M2 (2-hydroxypropyl). Metabolite M1 is less active than abrocitinib while metabolite M2 is as active as the parent. The pharmacologic activity of abrocitinib is attributable to the unbound exposure of parent molecule (~60%) as well as M1 (~10%) and M2 (~30%) in systemic circulation. The sum of unbound exposures of abrocitinib, M1 and M2, each expressed in molar units and adjusted for relative potencies, is referred to as the combined exposure of abrocitinib and its two active metabolites, M1 and M2.

Excretion

After a single radiolabeled abrocitinib dose, less than 1% of the dose was excreted in urine as unchanged drug. The metabolites of abrocitinib, M1 and M2 are excreted predominantly in urine, and are substrates of OAT3 transporter.

Specific Populations

Body weight, sex, race, and age did not have a clinically meaningful effect on CIBINQO exposure.

Patients with Renal Impairment

In a renal impairment study, subjects with severe (eGFR <30 mL/min as estimated by MDRD equation) and moderate (eGFR 30–59 mL/min, MDRD) renal impairment had approximately 191% and 110% increase in the combined exposure (AUCinf,u) of abrocitinib and its active metabolites, M1 and M2, respectively, compared to subjects with normal renal function (eGFR ≥90 mL/min, MDRD). Based on these results, a clinically significant increase in the combined exposure of abrocitinib and its active metabolites, M1 and M2, is not expected in patients with mild renal impairment (eGFR 60 –89 mL/min, MDRD) [see Dosage and Administration (2.3) and Use in Specific Population (8.6)].

CIBINQO has not been studied in subjects on renal replacement therapy [see Dosage and Administration (2.3) and Use in Specific Population (8.6)]. In Phase 3 clinical trials, CIBINQO was not evaluated in subjects with atopic dermatitis with baseline creatinine clearance values less than 40 mL/min.

Patients with Hepatic Impairment

Subjects with mild hepatic impairment (Child Pugh A) had approximately 4% decrease in the combined exposure (AUCinf,u) of abrocitinib and its two active metabolites, M1 and M2, compared to subjects with normal hepatic function. Subjects with moderate hepatic impairment (Child Pugh B) had approximately 15% increase in the combined exposure (AUCinf,u) of abrocitinib and its two active metabolites, M1 and M2, compared to subjects with normal hepatic function. These changes are not clinically significant. In clinical trials, CIBINQO has not been studied in subjects with severe (Child Pugh C) hepatic impairment, or in subjects screened positive for active hepatitis B or hepatitis C [see Use in Specific Populations (8.7) and Warnings and Precautions (5.1)].

Drug Interaction Studies

Clinical Studies

The effect of coadministered drugs on the pharmacokinetics of abrocitinib is presented in Table 6.

Table 6. Change in Pharmacokinetics of the Combined Exposure of Abrocitinib and its Two Active Metabolites (M1 and M2) in the Presence of Coadministered Drugs
Coadministered Drugs | Regimen of Coadministered Drug | Dose of Abrocitinib | Ratio [Ratios for Cmax,u and AUCinf,u compare coadministration of the drug with abrocitinib versus administration of abrocitinib alone.] (90% Confidence Interval)
Coadministered Drugs | Regimen of Coadministered Drug | Dose of Abrocitinib | Cmax,u | AUCinf,u
Strong CYP2C19 and moderate CYP3A inhibitor: Fluvoxamine [see Drug Interactions (7.1)] | 50 mg once daily × 9 days | 100 mg | 1.33 (1.00–1.78) | 1.91 (1.74–2.10)
Strong CYP2C19, moderate CYP2C9 and CYP3A inhibitor: Fluconazole [see Drug Interactions (7.1)] | 400 mg on Day 1 and 200 mg on Days 2–7 | 100 mg | 1.23 (1.08–1.42) | 2.55 [When coadministered with Fluconazole, the systemic exposure of abrocitinib was approximately 4.8-fold higher compared to when abrocitinib is administered alone.] (2.42–2.69)
Strong CYP Enzymes Inducers: Rifampin [see Drug Interactions (7.1)] | 600 mg once daily × 8 days | 200 mg | 0.69 (0.50–0.94) | 0.44 (0.41–0.47)
OAT3 inhibitor: Probenecid [Drug interaction with OAT3 inhibitor is not clinically significant.] | 1,000 mg twice daily × 3 days | 200 mg | 1.30 (1.04–1.63) | 1.66 (1.52–1.80)

The effect of abrocitinib on the pharmacokinetics of coadministered drugs is presented in Table 7.

Table 7. Change in Pharmacokinetics of Coadministered Drugs in the Presence of Abrocitinib
Coadministered Drugs or In Vivo Markers of CYP Activity | Dose Regimen of Abrocitinib | Ratio [Ratios for Cmax and AUCinf compare coadministration of abrocitinib with the drug versus administration of the drug alone.] (90% Confidence Interval)
Coadministered Drugs or In Vivo Markers of CYP Activity | Dose Regimen of Abrocitinib | Cmax | AUCinf
Oral contraceptive: Ethinyl estradiol (EE) and levonorgestrel (LN) | 200 mg once daily × 9 days | EE: 1.07 (0.99, 1.15) LN: 0.86 (0.75, 0.97) | EE: 1.19 (1.12, 1.26) LN [AUClast of levonorgestrel was reported in lieu of AUCinf because the terminal phase of levonorgestrel was not well characterized.] : 0.98 (0.87, 1.10)
Sensitive CYP3A Substrate: Midazolam | 200 mg once daily × 7 days | 0.93 (0.84, 1.04) | 0.92 (0.86, 0.99)
Sensitive P-gp substrate: Dabigatran | 200 mg single dose | 1.40 (0.92, 2.13) | 1.53 (1.09, 2.15)
Sensitive BCRP and OAT3 substrate: Rosuvastatin | 200 mg once daily × 3 days | 0.99 (0.86, 1.14) | 1.02 (0.93, 1.12)
Sensitive MATE1/2K substrate: Metformin | 200 mg once daily × 2 days | 0.88 (0.81, 0.96) | 0.93 (0.85, 1.03)

Coadministration of dabigatran etexilate (a P-gp substrate), with a single dose of CIBINQO 200 mg increased dabigatran AUCinf and Cmax by approximately 53% and 40%, respectively, compared with administration alone. These increases in dabigatran exposure are not considered clinically significant change. However, appropriate dose titration of P-gp substrate where small concentration changes may lead to serious or life-threatening toxicities (e.g., digoxin) when coadministered with the CIBINQO would be needed.

In Vitro Studies

Cytochrome P450 (CYP) Enzymes: Abrocitinib and its metabolites M1 and M2 are not inhibitors or inducers of CYP1A2, CYP2B6, CYP2C8, CYP2C9, CYP2C19, CYP2D6, or CYP3A4.

Uridine diphosphate (UDP)-glucuronosyl transferase (UGT) Enzymes: Abrocitinib and its metabolites M1 and M2 are not inhibitors or inducers of UGT1A1, UGT1A4, UGT1A6, UGT1A9, or UGT2B7.

Transporter Systems: Abrocitinib is an inhibitor of organic cation transporter (OCT)1 but is not an inhibitor of organic anion transporting polypeptide (OATP)1B1/1B3, bile salt export pump (BSEP), OAT1 or OCT2.

12.5 Pharmacogenomics

Patients who are CYP2C19 poor metabolizers have little to no CYP2C19 enzyme function compared to CYP2C19 normal metabolizers that have fully functional CYP2C19 enzymes.

After single doses of abrocitinib, CYP2C19 poor metabolizers demonstrated dose-normalized AUC of abrocitinib values that were 2.3-fold higher when compared to CYP2C19 normal metabolizers. Approximately 3–5% of Whites and Blacks and 15 to 20% of Asians are CYP2C19 poor metabolizers [see Dosage and Administration (2.4) and Use in Specific Populations (8.8)].

13 NONCLINICAL TOXICOLOGY

13.1 Carcinogenesis, Mutagenesis, Impairment of Fertility

In a 2-year oral carcinogenicity study in rats, abrocitinib increased the incidence of benign thymomas in female rats at doses of 10 and 30 mg/kg/day (2.8 and 14 times the MRHD, respectively, based on AUC comparison). Abrocitinib was not carcinogenic in female rats at 3 mg/kg/day (0.6 times the MRHD based on AUC comparison) or male rats at doses up to 30 mg/kg/day (14 times the MRHD based on AUC comparison). Abrocitinib was not carcinogenic in Tg.rasH2 mice at oral doses up to 60 mg/kg/day in males and 75 mg/kg/day in females.

Abrocitinib was not mutagenic in the bacterial mutagenicity assay (Ames assay). Although abrocitinib was aneugenic in the in vitro TK6 micronucleus assay, abrocitinib was not aneugenic or clastogenic in an in vivo rat bone marrow micronucleus assay.

Abrocitinib did not impair male fertility at doses up to 70 mg/kg/day (26 times the MRHD based on AUC comparison) or female fertility at 10 mg/kg/day (2 times the MRHD based on AUC comparison). Abrocitinib impaired female fertility (reducing fertility index, corpora lutea, and implantation sites) at 70 mg/kg/day (29 times the MRHD based on AUC comparison). Impaired fertility in female rats reversed 1 month after cessation of abrocitinib administration.

14 CLINICAL STUDIES

The efficacy of CIBINQO as monotherapy and in combination with background topical corticosteroids was evaluated in 4 randomized, double-blind, placebo-controlled trials [Trial-AD-1 (NCT03349060), Trial-AD-2 (NCT03575871), Trial-AD-3 (NCT03720470), and Trial-AD-4 (NCT03796676)] in 1900 subjects (see Table 8). Trial-AD-1 and Trial-AD-2 enrolled adult and pediatric subjects 12 years of age and older. Trial-AD-3 enrolled only adults (≥18 years of age) and Trial-AD-4 enrolled only pediatric subjects 12 to less than 18 years of age. The trials enrolled subjects with moderate-to-severe atopic dermatitis as defined by Investigator’s Global Assessment (IGA) score ≥3, Eczema Area and Severity Index (EASI) score ≥16, body surface area (BSA) involvement ≥10%, and Peak Pruritus Numerical Rating Scale (PP-NRS) ≥4 at the baseline visit prior to randomization.

Baseline Characteristics

In Trial-AD-1, Trial-AD-2, and Trial-AD-3, 53% of subjects were male, 69% of subjects were white, 64% of subjects had a baseline IGA score of 3 (moderate AD), and 36% of subjects had a baseline IGA score of 4 (severe AD). The baseline mean EASI score was 30. The baseline mean age was 36 years old with 8% of subjects 12 to less than 18 years old and 92% of subjects 18 years of age or older. Subjects in these trials were those who had inadequate response to previous topical therapy or were subjects for whom topical treatments were medically inadvisable or who had received systemic therapies including dupilumab. In each of the trials, over 40% of subjects had prior exposure to systemic therapy. In Trial-AD-1 and Trial-AD-2, 6% of the subjects had received dupilumab, whereas prior use of dupilumab was not allowed in Trial-AD-3.

In Trial-AD-4, 49% of subjects were female, 56% of subjects were White, 33% of subjects were Asian and 6% of subjects were Black. The median age was 15 years and the proportion of subjects with severe atopic dermatitis (IGA of 4) was 38%.

Trial Designs and Endpoints

Trial-AD-1, Trial-AD-2, Trial-AD-3, and Trial-AD-4 assessed the co-primary endpoints of IGA and EASI-75 responses at Week 12. The designs of the trials are summarized in Table 8.

Table 8. Summary of Clinical Trial Designs
Study Name (regimen type) Treatment Duration | Population (number of randomized and dosed subjects) | Treatment Arms | Co-Primary Endpoints
Trial-AD-1 (monotherapy); 12 weeks | Subjects 12 years of age or older (387) | Oral administration of:; - CIBINQO 200 mg QD - CIBINQO 100 mg QD - Placebo | - IGA response [IGA response was based on IGA score of clear (0) or almost clear (1) (on a 5-point scale) and a reduction from baseline of ≥2 points.] at Week 12 - EASI-75 [EASI-75 was based on ≥75% improvement in EASI from baseline.] at Week 12
Trial-AD-2 (monotherapy); 12 weeks | Subjects 12 years of age or older (391) | Oral administration of:; - CIBINQO 200 mg QD - CIBINQO 100 mg QD - Placebo | - IGA response [IGA response was based on IGA score of clear (0) or almost clear (1) (on a 5-point scale) and a reduction from baseline of ≥2 points.] at Week 12 - EASI-75 [EASI-75 was based on ≥75% improvement in EASI from baseline.] at Week 12
Trial-AD-3 (combination therapy); 16 weeks | Subjects 18 years of age or older (837) | Oral administration of:; - CIBINQO 200 mg QD - CIBINQO 100 mg QD - Placebo; Subcutaneous administration of:; - Dupilumab 300 mg Q2W SC [Dupilumab treatment in Trial-AD-3: An initial dose of 600 mg on day 1, followed by 300 mg Q2W.]; All subjects received background topical corticosteroids | - IGA response [IGA response was based on IGA score of clear (0) or almost clear (1) (on a 5-point scale) and a reduction from baseline of ≥2 points.] at Week 12 - EASI-75 [EASI-75 was based on ≥75% improvement in EASI from baseline.] at Week 12
Trial-AD-4; (combination therapy); 12 weeks | Subjects 12 to less than 18 years of age (285) | Oral administration of:; - CIBINQO 200 mg QD - CIBINQO 100 mg QD - Placebo; All subjects received background topical corticosteroids | - IGA response [IGA response was based on IGA score of clear (0) or almost clear (1) (on a 5-point scale) and a reduction from baseline of ≥2 points.] at Week 12 - EASI-75 [EASI-75 was based on ≥75% improvement in EASI from baseline.] at Week 12
Abbreviations: EASI=Eczema Area and Severity Index; IGA=Investigator’s Global Assessment; QD=once daily; Q2W=once every 2 weeks.

Clinical Response

Monotherapy Trials

The results of the CIBINQO monotherapy trials (Trial-AD-1 and Trial-AD-2) are presented in Table 9.

Table 9. Efficacy Results of CIBINQO Monotherapy at Week 12 in Subjects 12 Years of Age and Older with Moderate-to-Severe AD (Trial-AD-1 and Trial-AD-2)
 | Trial-AD-1 |  |  | Trial-AD-2
 | CIBINQO |  | Placebo N=77 | CIBINQO |  | Placebo N=78
 | 200 mg QD N=154 | 100 mg QD N=156 | Placebo N=77 | 200 mg QD N=155 | 100 mg QD N=158 | Placebo N=78
IGA 0 or 1 [IGA responders were subjects with IGA score of clear (0) or almost clear (1) (on a 5-point scale) and a reduction from baseline of ≥2 points.] | 44% | 24% | 8% | 38% | 28% | 9%
Difference; from Placebo (95% CI) | 36% (26%, 46%) | 16% (7%, 25%) | - | 29% (19%, 39%) | 19% (9%, 29%) | -
EASI-75 [EASI -75 responders were patients with ≥75% improvement in EASI from baseline.] | 62% | 40% | 12% | 61% | 44% | 10%
Difference; from Placebo (95% CI) | 51% (40%, 61%) | 28% (18%, 39%) | - | 50% (40%, 61%) | 33% (23%, 44%) | -
Abbreviations: CI=confidence interval; EASI=Eczema Area and Severity Index; IGA=Investigator Global Assessment; QD=once daily.

The proportion of subjects achieving PP-NRS4 at Week 2 (defined as an improvement of ≥4 points from baseline in PP-NRS) was higher in subjects treated with CIBINQO monotherapy 200 mg once daily (28% in Trial-AD-1 and 24% in Trial-AD-2) and 100 mg once daily (11% in both trials) compared to placebo (2% in both trials).

A higher proportion of subjects in the CIBINQO monotherapy 100 mg or 200 mg once daily arms compared to placebo achieved improvement in itching at Week 12.

Combination Therapy Trials

The results of CIBINQO in combination with background topical corticosteroids in subjects 18 years of age and older (Trial-AD-3) are presented in Table 10.

Table 10. Efficacy Results of CIBINQO with Concomitant Topical Corticosteroids at Week 12 in Subjects 18 Years of Age and Older with Moderate-to-Severe AD (Trial-AD-3)
% Responders | CIBINQO |  | Placebo N=131
% Responders | 200 mg QD N=226 | 100 mg QD N=238 | Placebo N=131
IGA 0 or 1 [IGA responders were subjects with IGA score of clear (0) or almost clear (1) (on a 5-point scale) and a reduction from baseline of ≥2 points.] at Week 12 | 47% | 36% | 14%
Difference from Placebo (95% CI) | 34% (25%, 42%) | 23% (15%, 31%) | -
EASI-75 [EASI-75 responders were subjects with ≥75% improvement in EASI, from baseline.] at Week 12 | 68% | 58% | 27%
Difference from Placebo (95% CI) | 41% (32%, 51%) | 32% (22%, 41%) | -
Abbreviations: CI=confidence interval; EASI=Eczema Area and Severity Index; IGA=Investigator Global Assessment; QD=once daily.

The proportions of subjects achieving PP-NRS4 at Week 2 was higher in subjects treated with CIBINQO 200 mg once daily (30%) and 100 mg once daily (14%) in combination with background medicated topical therapies compared to placebo (8%).

The results of CIBINQO in combination with background topical corticosteroids for pediatric subjects 12 to less than 18 years of age (Trial-AD-4) are presented in Table 11.

Table 11. Efficacy Results of CIBINQO with Concomitant Topical Corticosteroids at Week 12 in Pediatric Subjects 12 to less than 18 Years of Age with Moderate-to-Severe AD (Trial-AD-4)
% Responders | CIBINQO |  | Placebo; N=95
% Responders | 200 mg QD; N=94 | 100 mg QD; N=95 | Placebo; N=95
IGA 0 or 1 [IGA responders were patients with IGA score of clear (0) or almost clear (1) (on a 5-point scale) and a reduction from baseline of ≥2 points.] | 46% | 39% | 24%
Difference from Placebo; (95% CI) | 21%; (8%, 34%) | 15%; (2%, 28%) | -
EASI-75 [EASI-75 responders were patients with ≥75% improvement in EASI from baseline.] | 71% | 64% | 41%
Difference from Placebo; (95% CI) | 29%; (16%, 43%) | 23%; (10%, 36%) | -
Abbreviations: CI=confidence interval; EASI=Eczema Area and Severity Index; IGA=Investigator Global Assessment; N=number of patients treated; QD=once daily.

The proportion of pediatric subjects 12 to less than 18 years of age achieving PP-NRS4 at Week 2 in Trial-AD-4 was higher with CIBINQO 200 mg once daily (25%) and 100 mg once daily (13%) compared to placebo (8%).

A higher proportion of subjects in the CIBINQO 200 mg once daily arm compared to placebo achieved improvement in itching at Week 12.

Subgroup Analysis (Monotherapy Trials and the Combination Therapy Trial in Subjects 18 Years of Age and Older)

Examination of age, gender, race, weight, and previous systemic AD therapy treatment did not identify differences in response to CIBINQO 100 mg or 200 mg once daily among these subgroups in Trial-AD-1, Trial-AD-2, and Trial-AD-3.

16 HOW SUPPLIED/STORAGE AND HANDLING

CIBINQO is supplied as:

Dosage Form | Strength | Description | Bottle Size (number of tablets) | NDC Number
Tablets | 50 mg | Pink, oval tablet debossed with "PFE" on one side and "ABR 50" on the other. | 30 count bottle | 0069-0235-30
Tablets | 100 mg | Pink, round tablet debossed with "PFE" on one side and "ABR 100" on the other. | 30 count bottle | 0069-0335-30
Tablets | 200 mg | Pink, oval tablet debossed with "PFE" on one side and "ABR 200" on the other. | 30 count bottle | 0069-0435-30

STORAGE AND HANDLING

Store CIBINQO at 20°C to 25°C (68°F to 77°F), excursions permitted between 15°C to 30°C (59°F to 86°F). Keep in original package. The container closure system is child resistant.

17 PATIENT COUNSELING INFORMATION

Advise the patient to read the FDA-approved patient labeling (Medication Guide).

Pregnancy Registry

Advise patients to report their pregnancy to 1-877-311-3770 [see Use in Specific Populations (8.1)].

Serious Infections

Inform patients that they may develop infections when taking CIBINQO. Instruct patients to tell their healthcare provider if they develop any signs or symptoms of an infection [see Warnings and Precautions (5.1)].

Advise patients that the risk of herpes zoster is increased in patients treated with CIBINQO and some cases can be serious [see Warnings and Precautions (5.1)].

Malignancies

Inform patients that CIBINQO may increase their risk of certain cancers, including skin cancers. Periodic skin examinations are recommended while using CIBINQO. Advise patients that exposure to sunlight and UV light should be limited by wearing protective clothing and using a broad-spectrum sunscreen [see Warnings and Precautions (5.3)].

Major Adverse Cardiovascular Events

Inform patients that CIBINQO may increase their risk of major adverse cardiovascular events (MACE) including myocardial infarction, stroke, and cardiovascular death. Instruct all patients, especially current or past smokers or patients with other cardiovascular risk factors, to be alert for the development of signs and symptoms of cardiovascular events [see Warnings and Precautions (5.4)].

Thrombosis

Advise patients that events of DVT and PE have been reported in clinical trials with CIBINQO. Instruct patients to seek immediate medical attention if they develop any signs or symptoms of a DVT or PE [see Warnings and Precautions (5.5)].

Laboratory Abnormalities

Inform patients that CIBINQO may affect certain lab tests, and that blood tests are required before and during CIBINQO treatment [see Dosage and Administration (2.1) and Warnings and Precautions (5.6)].

Immunizations

Advise patients that vaccination with live vaccines is not recommended during CIBINQO treatment and immediately prior to or after CIBINQO treatment. Instruct patients to inform the healthcare practitioner that they are taking CIBINQO prior to a potential vaccination [see Warnings and Precautions (5.7)].

Retinal Detachment

Inform patients that retinal detachment has been reported in clinical trials for atopic dermatitis in patients who received CIBINQO. Advise patients to immediately inform their healthcare provider if they develop any sudden changes in vision while receiving CIBINQO [see Adverse Reactions (6.1)].

Infertility

Advise patients who can become pregnant that CIBINQO may impair fertility [see Use in Specific Populations (8.3)].

Lactation

Advise patients not to breastfeed during treatment with CIBINQO [see Use in Specific Populations (8.2)].

Administration

Advise patients not to chew, crush, or split CIBINQO tablets [see Dosage and Administration (2.7)].

This product's labeling may have been updated. For the most recent prescribing information, please visit www.pfizer.com.

For Medical Information about CIBINQO, please visit www.pfizermedinfo.com or call 1-800-438-1985.

LAB-1423-3.0

Medication Guide
CIBINQO (Si BINK oh)
(abrocitinib)
tablets, for oral use

What is the most important information I should know about CIBINQO?
CIBINQO may cause serious side effects, including:

1. Serious infections
CIBINQO is a medicine that affects your immune system. CIBINQO can lower the ability of your immune system to fight infections. Some people have had serious infections while taking CIBINQO or other similar medicines, including tuberculosis (TB), and infections caused by bacteria, fungi, or viruses that can spread throughout the body. Some people have been hospitalized or died from these infections.

- Your healthcare provider should test you for TB before starting treatment with CIBINQO.
- Your healthcare provider should watch you closely for signs and symptoms of TB during treatment with CIBINQO.

You should not start taking CIBINQO if you have any kind of infection unless your healthcare provider tells you it is okay.

You may be at a higher risk of developing shingles (herpes zoster).

Before starting CIBINQO, tell your healthcare provider if you:

- are being treated for an infection
- have had an infection that does not go away or that keeps coming back
- have diabetes, chronic lung disease, HIV, or a weak immune system
- have TB or have been in close contact with someone with TB
- have had shingles (herpes zoster)
- have had hepatitis B or hepatitis C
- live or have lived or have traveled to certain parts of the country (such as the Ohio and Mississippi River valleys and the Southwest) where there is an increased chance for getting certain kinds of fungal infections. These infections may happen or become more severe if you use CIBINQO. Ask your healthcare provider if you do not know if you have lived in an area where these infections are common.
- think you have an infection or have symptoms of an infection such as:

- fever, sweating, or chills
- muscle aches
- cough or shortness of breath

- blood in your phlegm
- weight loss
- warm, red, or painful skin or sores on your body

- diarrhea or stomach pain
- burning when you urinate or urinating more often than usual
- feeling very tired

After starting CIBINQO, call your healthcare provider right away if you have any symptoms of an infection. CIBINQO can make you more likely to get infections or make any infections that you have worse. If you get a serious infection, your healthcare provider may stop treatment with CIBINQO until your infection is controlled.

2. Increased risk of death in people 50 years of age and older who have at least 1 heart disease (cardiovascular) risk factor and are taking a medicine in the class of medicines called Janus kinase (JAK) inhibitors. CIBINQO is a JAK inhibitor medicine.

3. Cancer and immune system problems
CIBINQO may increase your risk of certain cancers by changing the way your immune system works.

- Lymphoma and other cancers, including skin cancers, can happen in people taking CIBINQO.
- People taking a medicine in the class of medicines called Janus kinase (JAK) inhibitors have a higher risk of certain cancers including lymphoma and lung cancer, especially if you are a current or past smoker.
- Follow your healthcare provider's advice about having your skin checked for skin cancer during treatment with CIBINQO. Limit the amount of time you spend in sunlight. Avoid using tanning beds or sunlamps. Wear protective clothing when you are in the sun and use a sunscreen with a high protection factor (SPF 30 and above). This is especially important if your skin is very fair or of you have a family history of skin cancer.

Tell your healthcare provider if you have ever had any type of cancer.

4. Increased risk of major cardiovascular events such as heart attack, stroke or death in people 50 years of age and older who have at least 1 heart disease (cardiovascular) risk factor and taking a medicine in the class of medicines called JAK inhibitors, especially if you are a current or past smoker.
Some people taking CIBINQO have had major cardiovascular events.
Get emergency help right away if you develop any symptoms of a heart attack or stroke during treatment with CIBINQO, including:

- discomfort in the center of your chest that lasts for more than a few minutes, or that goes away and comes back
- severe tightness, pain, pressure, or heaviness in your chest, throat, neck, or jaw
- pain or discomfort in your arms, back, neck, jaw, or stomach
- weakness in one part or on one side of your body
- slurred speech
- shortness of breath with or without chest discomfort
- breaking out in a cold sweat
- nausea or vomiting
- feeling lightheaded

5. Blood clots
Blood clots in the veins of your legs (deep vein thrombosis, DVT) or lungs (pulmonary embolism, PE) can happen in some people taking CIBINQO. This may be life-threatening. Blood clots in the veins of the legs (deep vein thrombosis, DVT) and lungs (pulmonary embolism, PE) have happened more often in people who are 50 years of age and older and with at least 1 heart disease (cardiovascular) risk factor taking a medicine in the class of medicines called Janus kinase (JAK) inhibitors.

- Tell your healthcare provider if you have had blood clots in the veins of your legs or lungs in the past.
- Stop taking CIBINQO and get medical help right away if you have any signs and symptoms of blood clots during treatment with CIBINQO, including:
  - swelling, pain or tenderness in one or both legs
  - sudden, unexplained chest or upper back pain
  - shortness of breath or difficulty breathing

6. Changes in certain laboratory test results
Your healthcare provider should do blood tests before you start taking CIBINQO and during treatment with CIBINQO to check for the following:

- low lymphocyte count. Lymphocytes are white blood cells that help the body fight off infections.
- low neutrophil count. Neutrophils are white blood cells that help the body fight off infections.
- low red blood cell count. This may mean that you have anemia, which may make you feel weak and tired.
- low platelet count. Platelets help form clots and stop or prevent bleeding.

You should not take CIBINQO if your lymphocyte counts, neutrophil counts, red blood cell counts, or platelet counts are too low. Your healthcare provider may stop your CIBINQO treatment for a period of time if needed because of changes in these blood test results.

Increased cholesterol levels. You may also have increases in the amount of fat found in your blood. Your healthcare provider should check your cholesterol about 4 weeks after you start CIBINQO, and then as needed.

See "What are the possible side effects of CIBINQO?" for more information about side effects.

What is CIBINQO?
CIBINQO is a prescription medicine that is a Janus Kinase (JAK) inhibitor. CIBINQO is used to treat adults and children 12 years of age and older with moderate-to-severe atopic dermatitis (eczema) that did not respond to other treatment and is not well controlled with prescription therapies, including biologic medicines or when these medicines cannot be tolerated.

It is not known if CIBINQO is safe and effective in children under 12 years of age.

Who should not take CIBINQO?

Do not take CIBINQO if you take medicines that prevent blood clots (antiplatelet medicines), except for low-dose aspirin up to a dose of 81 mg each day during the first 3 months of CIBINQO treatment.

Before taking CIBINQO, tell your healthcare provider about all of your medical conditions, including if you:

- See "What is the most important information I should know about CIBINQO?"
- have an infection
- are a current or past smoker
- have had a heart attack, other heart problems, or stroke
- have kidney problems or liver problems
- have low platelet counts or white blood cell counts
- have high levels of fat in your blood (high cholesterol)
- have any eye problems, including cataracts or retinal detachment.
- have recently received or are scheduled to receive an immunization (vaccine). People who take CIBINQO should not receive live vaccines.
- are pregnant or plan to become pregnant. It is not known if CIBINQO will harm your unborn baby.
  - Pregnancy Exposure Registry. Pfizer has a registry for women who take CIBINQO during pregnancy. The purpose of this registry is to check the health of you and your baby. If you are pregnant or become pregnant during treatment with CIBINQO, talk to your healthcare provider about how you can join this pregnancy registry, or you may contact the registry at 1-877-311-3770 or www.cibinqopregnancyregistry.com.
- are breastfeeding or plan to breastfeed. It is not known if CIBINQO passes into your breast milk. You and your healthcare provider should decide if you will take CIBINQO or breastfeed. You should not do both.

Tell your healthcare provider about all the medicines you take, including prescription and over-the-counter medicines, vitamins, and herbal supplements. CIBINQO and other medicines may affect each other causing side effects.
Especially tell your healthcare provider if you take aspirin or any antiplatelet therapies (See the "Who should not take CIBINQO?" section). Ask your healthcare provider if you are unsure.
Know the medicines you take. Keep a list of them to show your healthcare provider and pharmacist whenever you get a new medicine.

How should I take CIBINQO?

- Take CIBINQO exactly as your healthcare provider tells you to take it.
- Take CIBINQO 1 time each day, at about the same time each day.
- Swallow CIBINQO tablets whole with water. Do not split, crush, or chew the tablets.
- You can take CIBINQO with or without food.
- CIBINQO can be used with or without prescribed topical steroid medicines for atopic dermatitis. Prescribed topical medicine are lotions, creams, or ointments applied to your skin.
- If you miss a dose, take the dose as soon as possible. If it is less than 12 hours before the next dose, skip the dose. Take the next dose at your usually scheduled time.
- In case of overdose, get medical help or contact a Poison Center expert right away at 1-800-222-1222. Advice is also available online at poisonhelp.org.

What are the possible side effects of CIBINQO?
CIBINQO may cause serious side effects.

See "What is the most important information I should know about CIBINQO?"

The most common side effects of CIBINQO include:

- See "What is the most important information I should know about CIBINQO."

- common cold
- nausea
- headache
- herpes simplex including cold sores
- increased blood level of creatine phosphokinase
- dizziness
- urinary tract infection
- tiredness
- acne
- vomiting

- mouth and throat pain
- flu
- stomach flu
- bacterial skin infection (impetigo)
- high blood pressure
- allergic skin rash to something you came into contact with
- stomach-area pain
- shingles
- low platelet count

Separation or tear to the lining of the back part of the eye (retinal detachment) has happened in people with atopic dermatitis treated with CIBINQO. Call your healthcare provider right away if you have any sudden changes in your vision during treatment with CIBINQO.
CIBINQO may cause fertility problems in females, which may affect your ability to get pregnant. Talk to your healthcare provider if you have concerns about fertility.

These are not all the possible side effects of CIBINQO.
Call your doctor for medical advice about side effects. You may report side effects to FDA at 1-800-FDA-1088.
You may also report side effects to Pfizer at 1-800-438-1985.

How should I store CIBINQO?

- Store CIBINQO at room temperature between 68°F to 77°F (20°C to 25°C).
- Store CIBINQO in the original package.
- The container has a child resistant closure.

Keep CIBINQO and all medicines out of the reach of children.

General information about the safe and effective use of CIBINQO.
Medicines are sometimes prescribed for purposes other than those listed in a Medication Guide. Do not use CIBINQO for a condition for which it was not prescribed. Do not give CIBINQO to other people, even if they have the same symptoms you have. It may harm them.

You can ask your pharmacist or healthcare provider for information about CIBINQO that is written for health professionals.

What are the ingredients in CIBINQO?
Active ingredient: abrocitinib
Inactive ingredients: dibasic calcium phosphate anhydrous, hypromellose, iron oxide red, lactose monohydrate, Macrogol, magnesium stearate, microcrystalline cellulose, sodium starch glycolate, titanium dioxide, and triacetin.

LAB-1424-3.0

This Medication Guide has been approved by the U.S. Food and Drug Administration. Approved: 12/2023

PRINCIPAL DISPLAY PANEL - 50 mg Tablet Bottle Label

PROFESSIONAL SAMPLE-NOT FOR SALE
ALWAYS DISPENSE WITH
MEDICATION GUIDE

Pfizer
NDC 63539-236-14

CIBINQO™
(abrocitinib) tablets

50 mg

Do not crush, split, or chew the tablets.

14 Tablets
Rx only

PRINCIPAL DISPLAY PANEL - 100 mg Tablet Bottle Label

PROFESSIONAL SAMPLE-NOT FOR SALE
ALWAYS DISPENSE WITH
MEDICATION GUIDE

Pfizer
NDC 63539-336-14

CIBINQO™
(abrocitinib) tablets

100 mg

Do not crush, split, or chew the tablets.

14 Tablets
Rx only

PRINCIPAL DISPLAY PANEL - 200 mg Tablet Bottle Label

PROFESSIONAL SAMPLE-NOT FOR SALE
ALWAYS DISPENSE WITH
MEDICATION GUIDE

Pfizer
NDC 63539-436-14

CIBINQO™
(abrocitinib) tablets

200 mg

Do not crush, split, or chew the tablets.

14 Tablets
Rx only